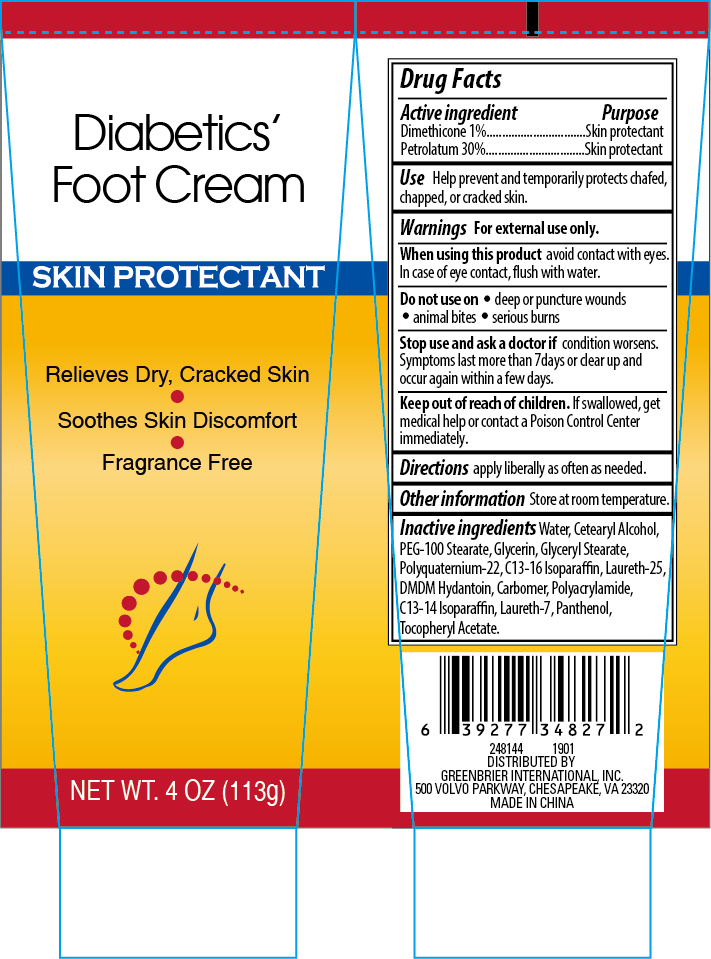 DRUG LABEL: Diabetics Foot Cream
NDC: 33992-3037 | Form: LOTION
Manufacturer: Greenbrier International, Inc.
Category: otc | Type: HUMAN OTC DRUG LABEL
Date: 20181219

ACTIVE INGREDIENTS: PETROLATUM 30 g/100 g; DIMETHICONE 1 g/100 g
INACTIVE INGREDIENTS: GLYCERYL MONOSTEARATE; WATER; GLYCERIN; POLYACRYLAMIDE (1500 MW); DMDM HYDANTOIN; C13-16 ISOPARAFFIN; LAURETH-7; POLYQUATERNIUM-22 (4500 MPA.S); .ALPHA.-TOCOPHEROL ACETATE, D-; CETOSTEARYL ALCOHOL; CARBOXYPOLYMETHYLENE; PANTHENOL; PEG-100 STEARATE; LAURETH-25; C13-14 ISOPARAFFIN

Diabetics' Foot Cream 4 oz

Active Ingredient Purpose

Dimethicone 1% ...... Skin Protectant

Petrolatum 30%........Skin Protectant

PURPOSE

Skin protectant

Keep out of reach of children. If swallowed, get medical help or contact a Poison Control Center immediately.

INDICATIONS AND USAGE

Use help prevent and temporarily protets chafed, chapped, or cracked skin.

Warnings For external use only.

When using this product avoid contact with eyes. In case of eye contact, flush with water.

Do not use on

- deep or puncture wounds
- animal bites
- serious burns

Stop use and ask a doctor if condition worsens. Symptoms last more than 7 days or clear up and occur again within a few days.

DOSAGE AND ADMINISTRATION

Directions apply liberally as often as needed.

Other information Store at room temperature.

DISTRIBUTED BY:

GREENBRIER INTERNATIONAL, INC.

500 VOLVO PARKWAY, CHESAPEAKE, VA 23320

MADE IN CHINA

INACTIVE INGREDIENT

Inactive Ingredients water, ceterayl alcohol, PEG-100 stearate, glycerin, glyceryl stearate, polyquaternium-22, c13-16 isoparaffin laureth-25,DMDM hydantoin, carbomer, polyacrylamide, c13-14 isoparaffin, laureth-7, panthenol, tocopheryl acetate